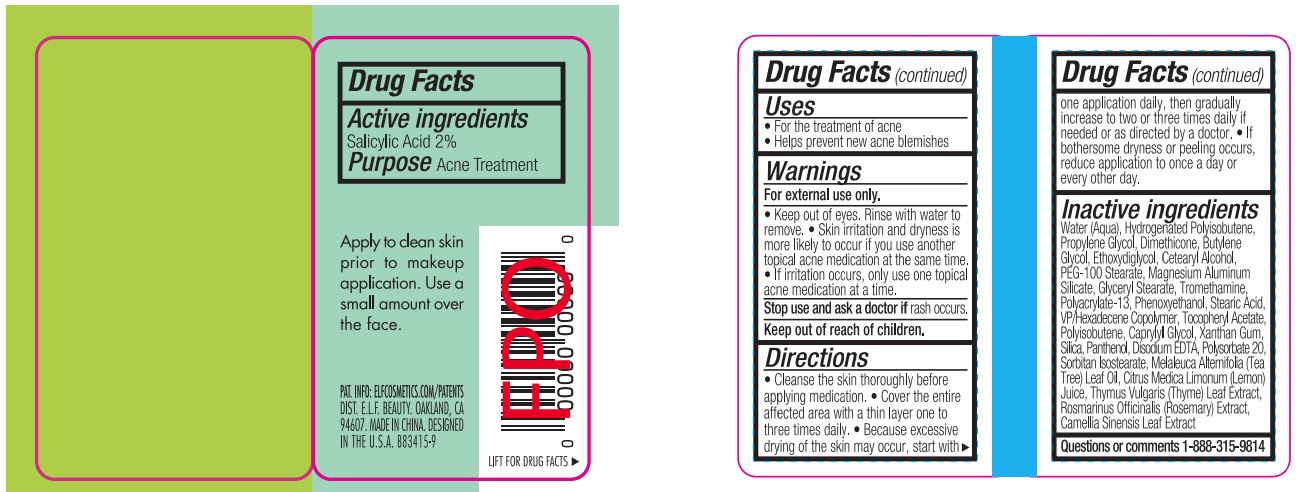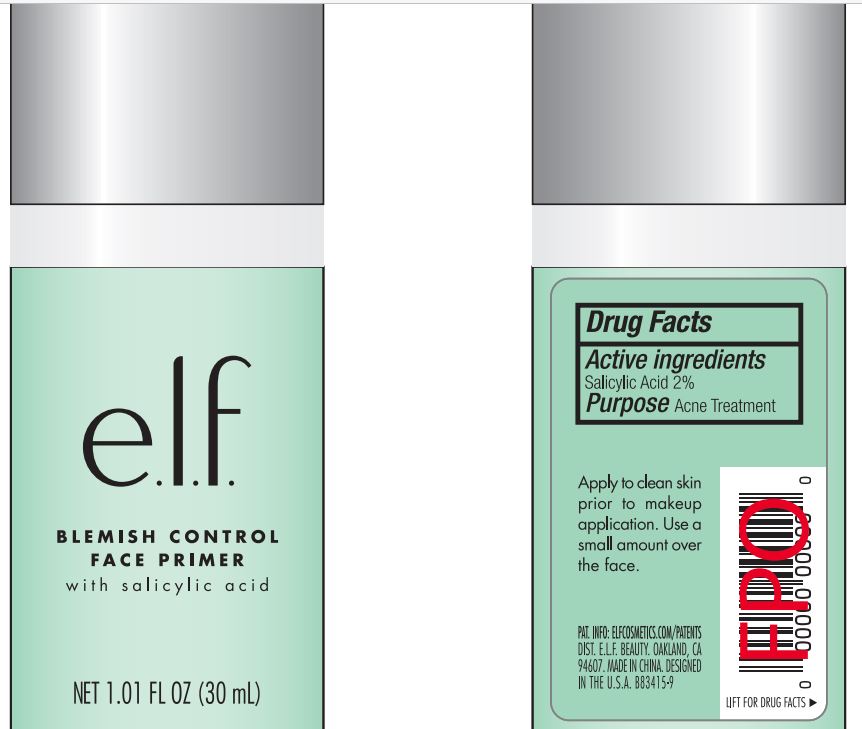 DRUG LABEL: ELF Blemish Control Face Primer Clear
NDC: 76354-210 | Form: CREAM
Manufacturer: e.l.f. Cosmetics, Inc
Category: otc | Type: HUMAN OTC DRUG LABEL
Date: 20241106

ACTIVE INGREDIENTS: SALICYLIC ACID 2 g/100 mL
INACTIVE INGREDIENTS: HYDROGENATED POLYBUTENE (370 MW); WATER; DIMETHICONE; BUTYLENE GLYCOL; MAGNESIUM ALUMINUM SILICATE; PROPYLENE GLYCOL; GLYCERYL STEARATE SE; PEG-100 STEARATE; TRIETHANOLAMINE HYDRIODIDE; POLYACRYLAMIDE (10000 MW); C13-14 ISOPARAFFIN; LAURETH-7; .ALPHA.-TOCOPHEROL ACETATE; STEARIC ACID; XANTHAN GUM; DISODIUM HEDTA; PANTHENOL; ROSMARINUS OFFICINALIS FLOWER; THYMUS VULGARIS LEAF; CAMELLIA SINENSIS WHOLE; CITRUS LIMON FRUIT OIL; CAPRYLYL GLYCOL; PHENOXYETHANOL

ELF Blemish Control Face Primer Clear

Active Ingredient:

Salicylic Acid 2.0%

Purpose:

Acne Treatment

Uses:

For the treatment of acne

Helps prevent new acne blemishes

Warning:

For external use only

When Using This Product:

Keep out of eyes, rinse with water to remove.

Skin irrittion and dryness is more likely to occur if you use another topical acne medications at the same time.

If irritation occurs, only use one topical acne medication at a time.

Stop use and ask a doctor If

rash occurs

Keep Out of Reach of Children

Directions:

Cleanse the skin thoroughly before applying medication.

Cover the entire affected area with a thin layer one to three times daily.

Because excessive drying of skin may occur, start with one application daily, then gradually increase to two or three times daily if needed or as directed by a doctor.

If bothersome dryness or peeling occurs, reduce application to once a day or every other day.

Inactive Ingredient:

Water, Hydrogenated Polyisobutene, Dimethicone, Butylene Glycol, Ethoxydiglycol, Propylene Glycol, Magnesium Aluminum Silicate, Cetearyl Alcohol, Glyceryl Stearate, PEG-100 Stearate, Tyiethanolamine, Polyacrylamide, C13-14 Isoparaffin, Laureth-7, VP/Hexadecene Coplymer, Tocopheryl Acetate (VE), Stearic Acid, Xanthan Gum, Silica, Disodium EDTA, Panthenol, Rosmarinus Officinalis (Rosemary) Extract, Thymus Vulgaris (Thyme) Extract, Camellia Sinensis Leaf Extract, Citrus Limon (Lemon) Peel Extract, Phenoxyethanol, Caprylyl Glycol